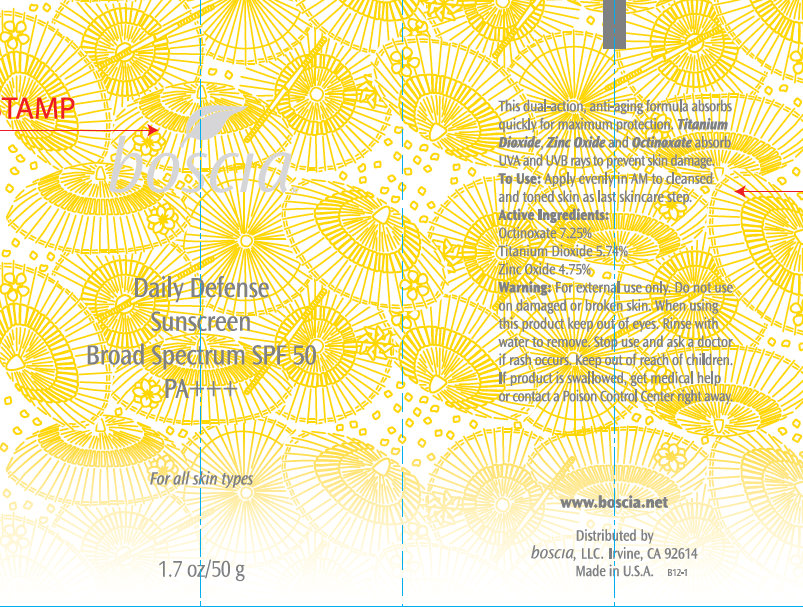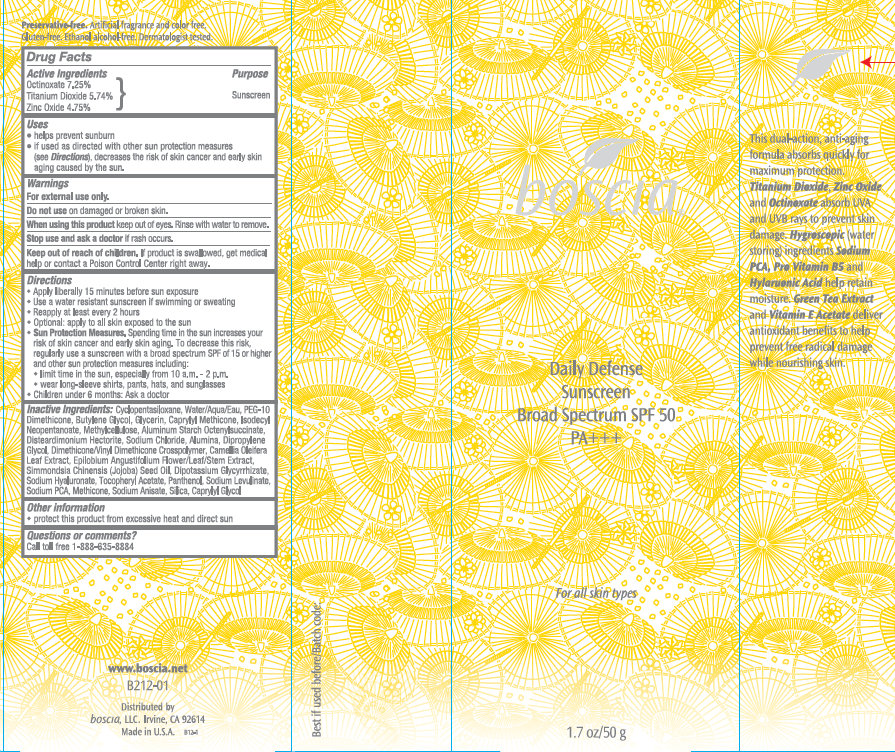 DRUG LABEL: Boscia Daily Defense Sunscreen Broad Spectrum SPF 50 PA
NDC: 76151-241 | Form: CREAM
Manufacturer: Boscia LLC
Category: otc | Type: HUMAN OTC DRUG LABEL
Date: 20231212

ACTIVE INGREDIENTS: OCTINOXATE 7.25 g/100 g; TITANIUM DIOXIDE 5.742 g/100 g; ZINC OXIDE 4.75 g/100 g
INACTIVE INGREDIENTS: CYCLOMETHICONE 5; WATER; BUTYLENE GLYCOL; GLYCERIN; CAPRYLYL TRISILOXANE; ISODECYL NEOPENTANOATE; ALUMINUM STARCH OCTENYLSUCCINATE; SODIUM CHLORIDE; ALUMINUM OXIDE; DIPROPYLENE GLYCOL; DIMETHICONE; CAMELLIA OLEIFERA LEAF; EPILOBIUM ANGUSTIFOLIUM FLOWERING TOP; JOJOBA OIL; GLYCYRRHIZINATE DIPOTASSIUM; HYALURONATE SODIUM; .ALPHA.-TOCOPHEROL ACETATE; PANTHENOL; SODIUM LEVULINATE; SODIUM PYRROLIDONE CARBOXYLATE; SODIUM ANISATE; SILICON DIOXIDE; CAPRYLYL GLYCOL

Boscia Daily Defense Sunscreen Broad Spectrum SPF 50 PA

Active Ingredients

Octinoxate 7.25% Titanium Dioxide 5.74% Zinc Oxide 4.75%

Purpose

Sunscreen

Uses

- helps prevent sunburn
- If used as directed with other sun protection measures (see Directions), decreases the risk of skin cancer and early skin aging caused by the sun.

Warnings

For external use only.

Do not use

on damaged or broken skin.

When using this product

keep out of eyes. Rinse with water to remove.

Stop use and ask a doctor

if rash occurs.

Keep out of reach of children

If product is swallowed, get medical help or contact a Poison Control Center right away.

Directions

- Apply liberally 15 minutes before sun exposure
- Use a water resistant sunscreen if swimming or sweating
- Reapply at least every 2 hours
- Optional: apply to all skin exposed to the sun
- Spending time in the sun increases your risk of skin cancer and early skin aging. To decrease this risk regularly use a sunscreen with a broadspectrum SPF of 15 or higher and another sun protection measures including: Sun Protection Measures.
- Limit time in the usn, especially from 10 a.m. - 2 p.m.
- wear long-sleeve shirts, pants, hats, and sunglasses.
- Children under 6 months: Ask a doctor

Inactive Ingredients:

Cyclopentasiloxane, Water/Aqua/Eau, PEG-10 Dimethicone, Butylene Glycol, Glycerin, Caprylyl Methicone, Isodecyl Neopentanoate, Methylcellulose, Aluminum Starch Octenylsuccinate, Disteardimonium Hectorite, Sodium Chloride, Alumina, Dipropylene Glycol, Dimethicone/Vinyl Dimethicone Crosspolymer, Camellia Oleifera Leaf Extract, Epilobium Angustifolium Flower/Leaf/Stem Extract, Simmondsia Chinensis (Jojoba) Seed Oil, Dipotassium Glycyrrhizate, Sodium Hyaluronate, Tocopheryl Acetate, Panthenol, Sodium Levulinate, Sodium PCA, Methicone, Sodium Anisate, Silica, Caprylyl Glycol.

Other information

- protect this product from excessive heat and sun

Questions or comments?

Call toll free 1-888-635-8884

This dual-action, anti-aging formula absorbs quickly for maximum protection. and absorb UVA and UVB rays to prevent skin damage. (water storing) ingredients and help certain moisture. and deliver antioxidant benefits to help prevent free radical damage while nourishing skin. Titanium Dioxide, Zinc Oxide Octinoxate Hygroscopic Sodium PCA, Pre Vitamin B5 Hylauronic Acid Green Tea Extract Vitamin E Acetate

Artificial fragrance and color free. Gluten-free. Ethanol alcohol-free. Dermatologist tested. www.boscia.net B212-01 Distributed by boscia, LLC. Irvine, CA 92614 Made in USA Preservative-free.

PACKAGE LABEL

boscia Daily Defense Sunscreen Broad Spectrum SPF 50 PA+++ 1.7 oz / 50 g For all skin types